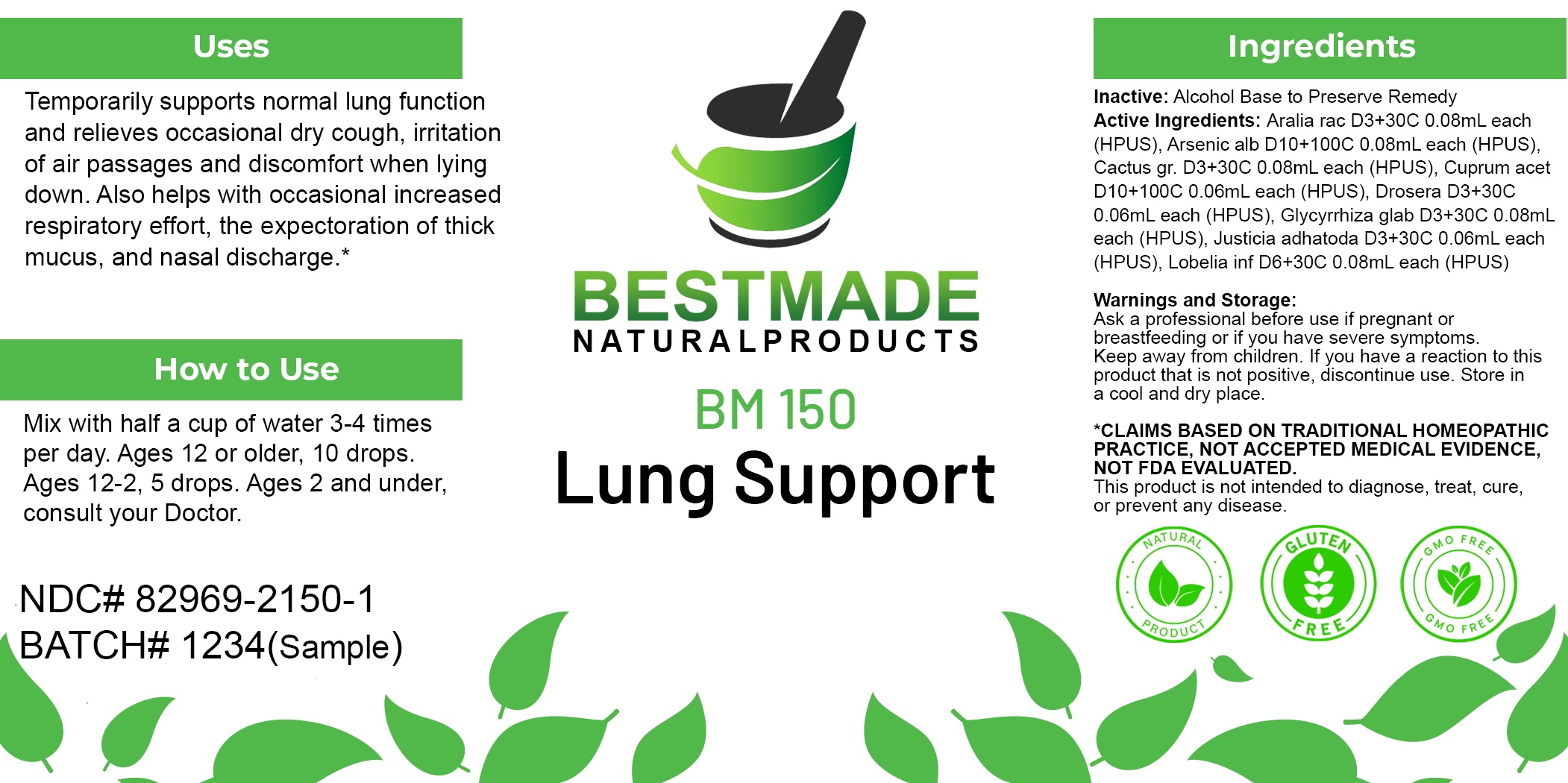 DRUG LABEL: Bestmade Natural Products BM150
NDC: 82969-2150 | Form: LIQUID
Manufacturer: Bestmade Natural Products
Category: homeopathic | Type: HUMAN OTC DRUG LABEL
Date: 20250218

ACTIVE INGREDIENTS: GLYCYRRHIZA GLABRA (LICORICE) ROOT POWDER 30 [hp_C]/30 [hp_C]; LOBELIA INFLATA WHOLE 30 [hp_C]/30 [hp_C]; DROSERA ROTUNDIFOLIA WHOLE 30 [hp_C]/30 [hp_C]; ARALIA RACEMOSA ROOT 30 [hp_C]/30 [hp_C]; CUPRIC ACETATE 30 [hp_C]/30 [hp_C]; ARSENIC TRIOXIDE 30 [hp_C]/30 [hp_C]; SELENICEREUS GRANDIFLORUS STEM 30 [hp_C]/30 [hp_C]; JUSTICIA ADHATODA LEAF 30 [hp_C]/30 [hp_C]
INACTIVE INGREDIENTS: ALCOHOL 30 [hp_C]/30 [hp_C]

BM150

DOSAGE AND ADMINISTRATION

How to Use

Mix with half a cup of water 3-4 times per day. Ages 12 or older, 10 drops. Ages 12-2, 5 drops. Ages 2 and under, consult your Doctor.

Inactive:

Alcohol Base to Preserve Product

ACTIVE INGREDIENTS

Aralia rac D3+30C 0.08mL each (HPUS), Arsenic alb D10+100C 0.08mL each (HPUS), Cactus gr. D3+30C 0.08mL each (HPUS), Cuprum acet D10+100C 0.06mL each (HPUS), Drosera D3+30C 0.06mL each (HPUS), Glycyrrhiza glab D3+30C 0.08mL each (HPUS), Justicia adhatoda D3+30C 0.06mL each (HPUS), Lobelia inf D6+30C 0.08mL each (HPUS)

Uses
Temporarily supports normal lung function and relieves occasional dry cough, irritation of air passages and discomfort when lying
down. Also helps with occasional increased respiratory effort, the expectoration of thick mucus, and nasal discharge.*

Uses
Temporarily supports normal lung function and relieves occasional dry cough, irritation of air passages and discomfort when lying
down. Also helps with occasional increased respiratory effort, the expectoration of thick mucus, and nasal discharge.*

KEEP OUT OF REACH OF CHILDREN

Warnings and Storage:

Ask a professional before use if pregnant or breastfeeding or if you have severe symptoms.

Keep away from children. If you have a reaction to this product that is not positive, discontinue use. Store in a cool and dry place

*CLAIMS BASED ON TRADITIONAL HOMEOPATHIC PRACTICE, NOT ACCEPTED MEDICAL EVIDENCE NOT FDA EVALUATED.
This product is not intended to diagnose, treat, cure, or prevent any disease.

Warnings and Storage:

Ask a professional before use if pregnant or breastfeeding or if you have severe symptoms.

Keep away from children. If you have a reaction to this product that is not positive, discontinue use. Store in a cool and dry place

*CLAIMS BASED ON TRADITIONAL HOMEOPATHIC PRACTICE, NOT ACCEPTED MEDICAL EVIDENCE NOT FDA EVALUATED.
This product is not intended to diagnose, treat, cure, or prevent any disease.

Entire package label